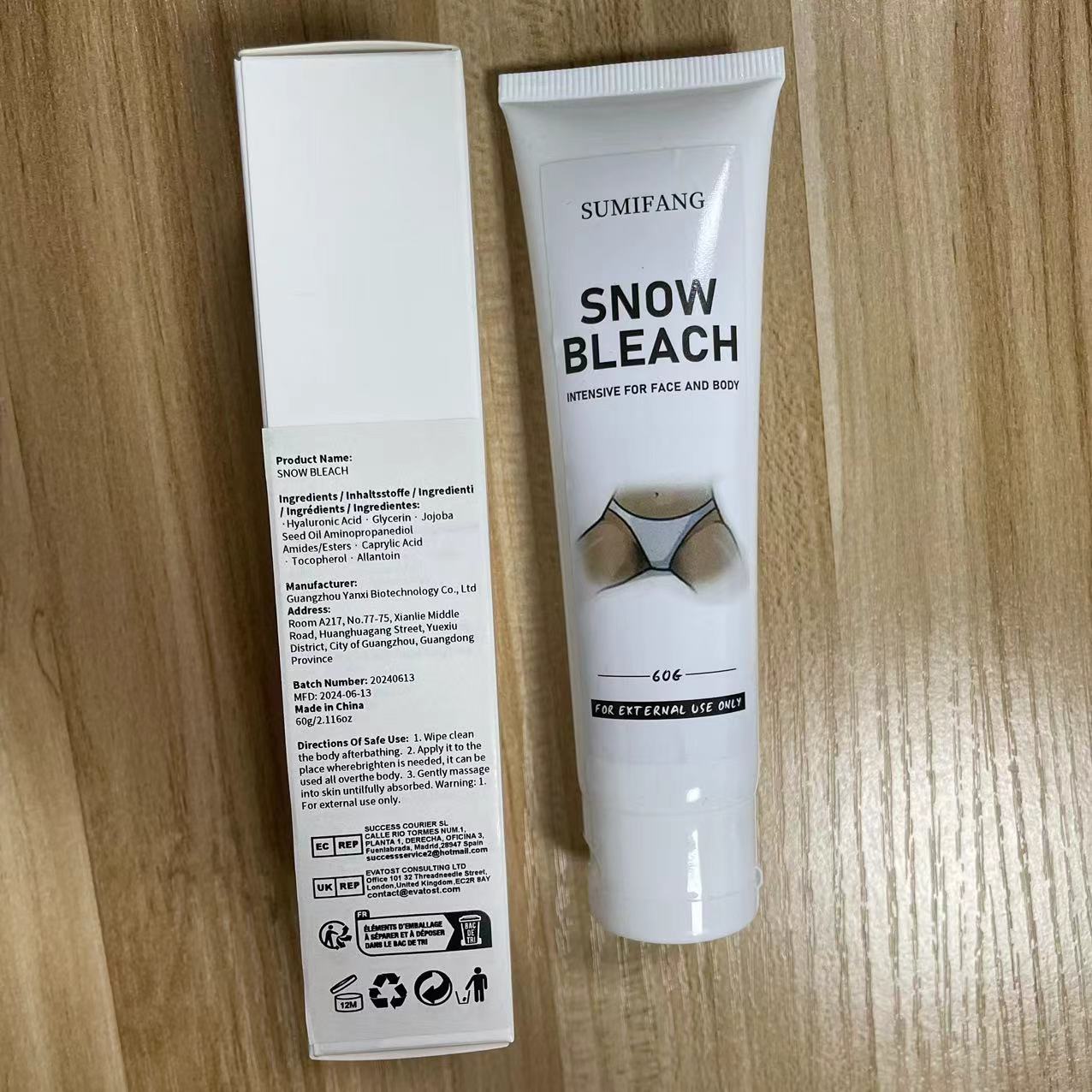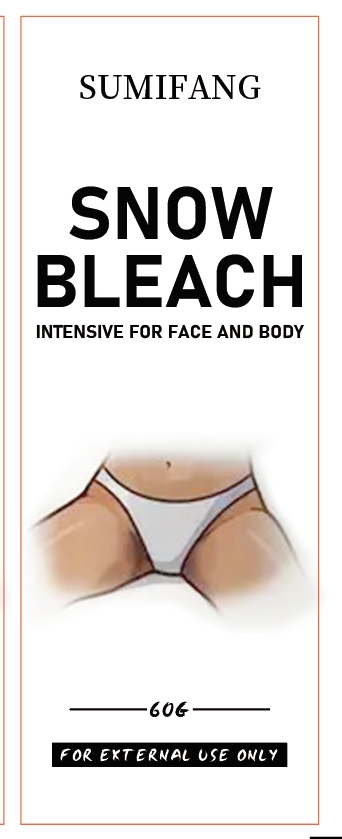 DRUG LABEL: SNOW BLEACH
NDC: 84025-042 | Form: CREAM
Manufacturer: Guangzhou Yanxi Biotechnology Co., Ltd
Category: otc | Type: HUMAN OTC DRUG LABEL
Date: 20240614

ACTIVE INGREDIENTS: GLYCERIN 5 mg/60 g; HYALURONIC ACID 3 mg/60 g
INACTIVE INGREDIENTS: WATER

DOSAGE AND ADMINISTRATION

use for body

WARNINGS

For external use only.

INACTIVE INGREDIENT

aqua

INDICATIONS AND USAGE

Massage over skin

Keep out of reach of children.

PURPOSE

moisturizing